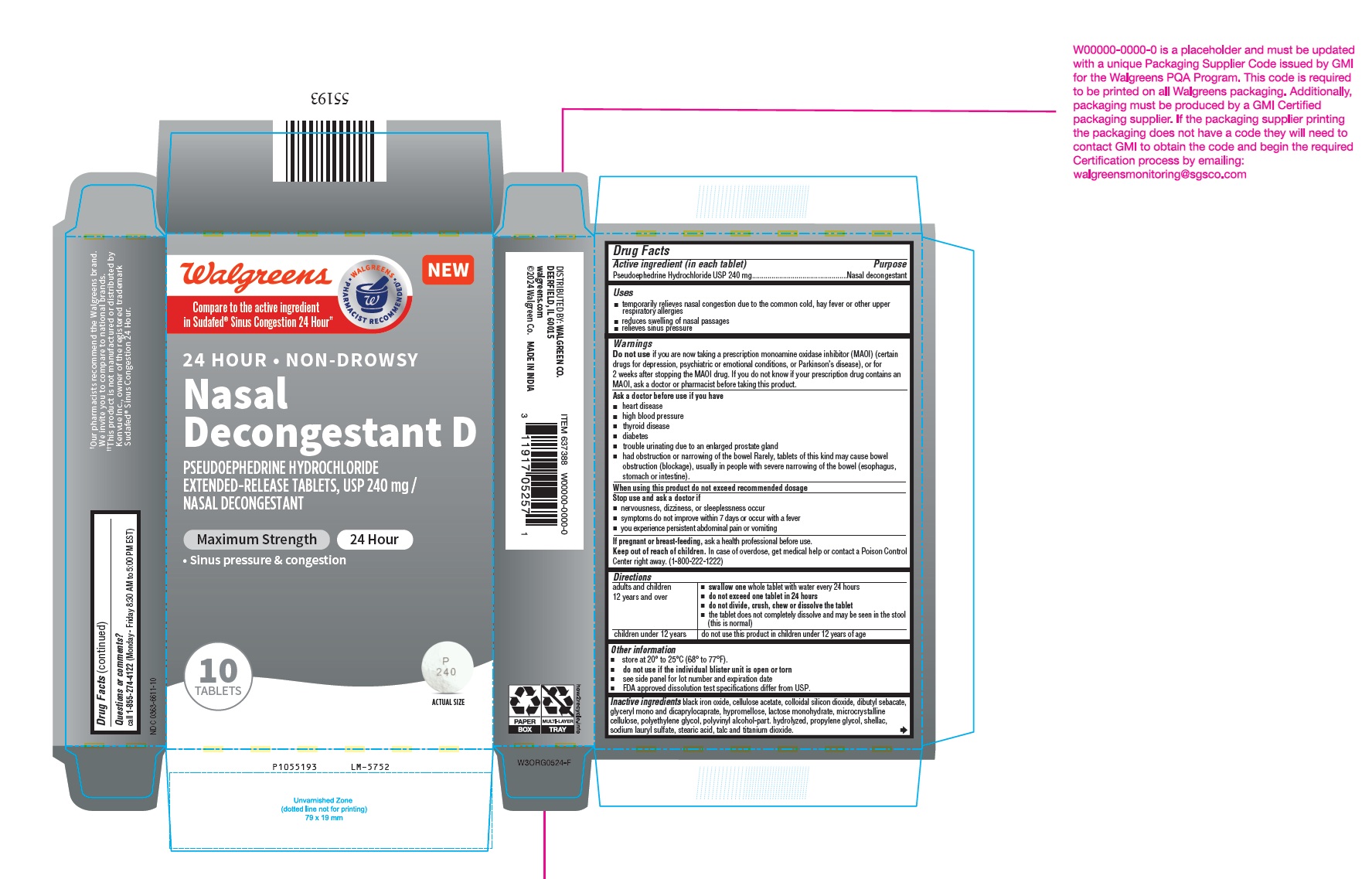 DRUG LABEL: Pseudoephedrine Hydrochloride
NDC: 0363-6611 | Form: TABLET, EXTENDED RELEASE
Manufacturer: WALGREEN CO.
Category: otc | Type: Human OTC Drug Label
Date: 20260203

ACTIVE INGREDIENTS: PSEUDOEPHEDRINE HYDROCHLORIDE 240 mg/1 1
INACTIVE INGREDIENTS: FERROSOFERRIC OXIDE; CELLULOSE ACETATE; SILICON DIOXIDE; DIBUTYL SEBACATE; GLYCERYL MONO- AND DICAPRYLOCAPRATE; HYPROMELLOSE 2208 (100000 MPA.S); HYPROMELLOSE 2910 (3 MPA.S); LACTOSE MONOHYDRATE; MICROCRYSTALLINE CELLULOSE; POLYETHYLENE GLYCOL 400; POLYVINYL ALCOHOL, UNSPECIFIED; PROPYLENE GLYCOL; SHELLAC; SODIUM LAURYL SULFATE; STEARIC ACID; TALC; TITANIUM DIOXIDE

Pseudoephedrine Hydrochloride Extended-Release Tablets, USP 240 mg

Drug Facts

Active ingredient (in each tablet)

Pseudoephedrine Hydrochloride USP 240 mg

Purpose

Nasal decongestant

Uses

- temporarily relieves nasal congestion due to the common cold, hay fever or other upper respiratory allergies
- reduces swelling of nasal passages
- relieves sinus pressure

Warnings

Do not use if you are now taking a prescription monoamine oxidase inhibitor (MAOI) (certain drugs for depression, psychiatric or emotional conditions, or Parkinson’s disease), or for 2 weeks after stopping the MAOI drug. If you do not know if your prescription drug contains an MAOI, ask a doctor or pharmacist before taking this product.

Ask a doctor before use if you have

- heart disease
- high blood pressure
- thyroid disease
- diabetes
- trouble urinating due to an enlarged prostate gland
- had obstruction or narrowing of the bowel Rarely, tablets of this kind may cause bowel obstruction (blockage), usually in people with severe narrowing of the bowel (esophagus, stomach or intestine).

When using this product do not exceed recommended dosage

Stop use and ask a doctor if

STOP USE

- nervousness, dizziness, or sleeplessness occur
- symptoms do not improve within 7 days or occur with a fever
- you experience persistent abdominal pain or vomiting

PREGNANCY OR BREAST FEEDING

If pregnant or breast-feeding, ask a health professional before use.

Keep out of reach of children.

In case of overdose, get medical help or contact a Poison Control Center right away. (1-800-222-1222)

Directions

adults and children 12 years and over | - swallow one whole tablet with water every 24 hours - do not exceed one tablet in 24 hours - do not divide, crush, chew or dissolve the tablet - the tablet does not completely dissolve and may be seen in the stool (this is normal)
children under 12 years | do not use this product in children under 12 years of age

Other information

- store at 20° to 25°C (68° to 77°F).
- do not use if the individual blister unit is open or torn
- see side panel for lot number and expiration date
- FDA approved dissolution test specifications differ from USP.

Inactive ingredients

black iron oxide, cellulose acetate, colloidal silicon dioxide, dibutyl sebacate, glyceryl mono and dicaprylocaprate, hypromellose, lactose monohydrate, microcrystalline cellulose, polyethylene glycol, polyvinyl alcohol-part. hydrolyzed, propylene glycol, shellac, sodium lauryl sulfate, stearic acid, talc and titanium dioxide.
Questions or comments?
call 1-855-274-4122 (Monday - Friday 8:30 AM to 5:00 PM EST)

DISTRIBUTED BY: WALGREEN CO.
DEERFIELD, IL 60015

MADE IN INDIA

PACKAGE LABEL-PRINCIPAL DISPLAY PANEL - 1 x 10 Blister Carton Label

Walgreens
NEW
Compare to the active ingredient
in Sudafed® Sinus Congestion 24 Hour††
24 HOUR • NON-DROWSY
Nasal
Decongestant D
PSEUDOEPHEDRINE HYDROCHLORIDE
EXTENDED-RELEASE TABLETS, USP 240 mg /
NASAL DECONGESTANT
Maximum Strength 24 Hour
• Sinus pressure & congestion
10
TABLETS ACTUAL SIZE